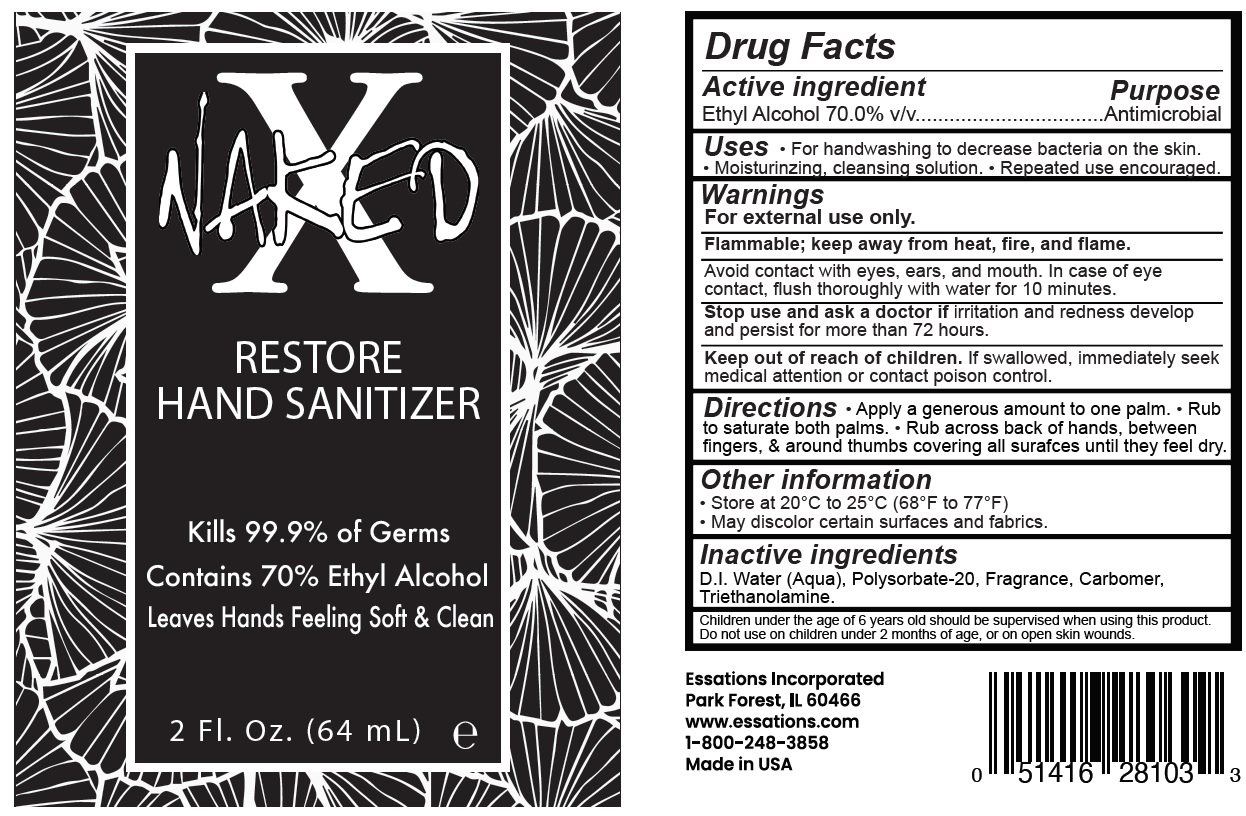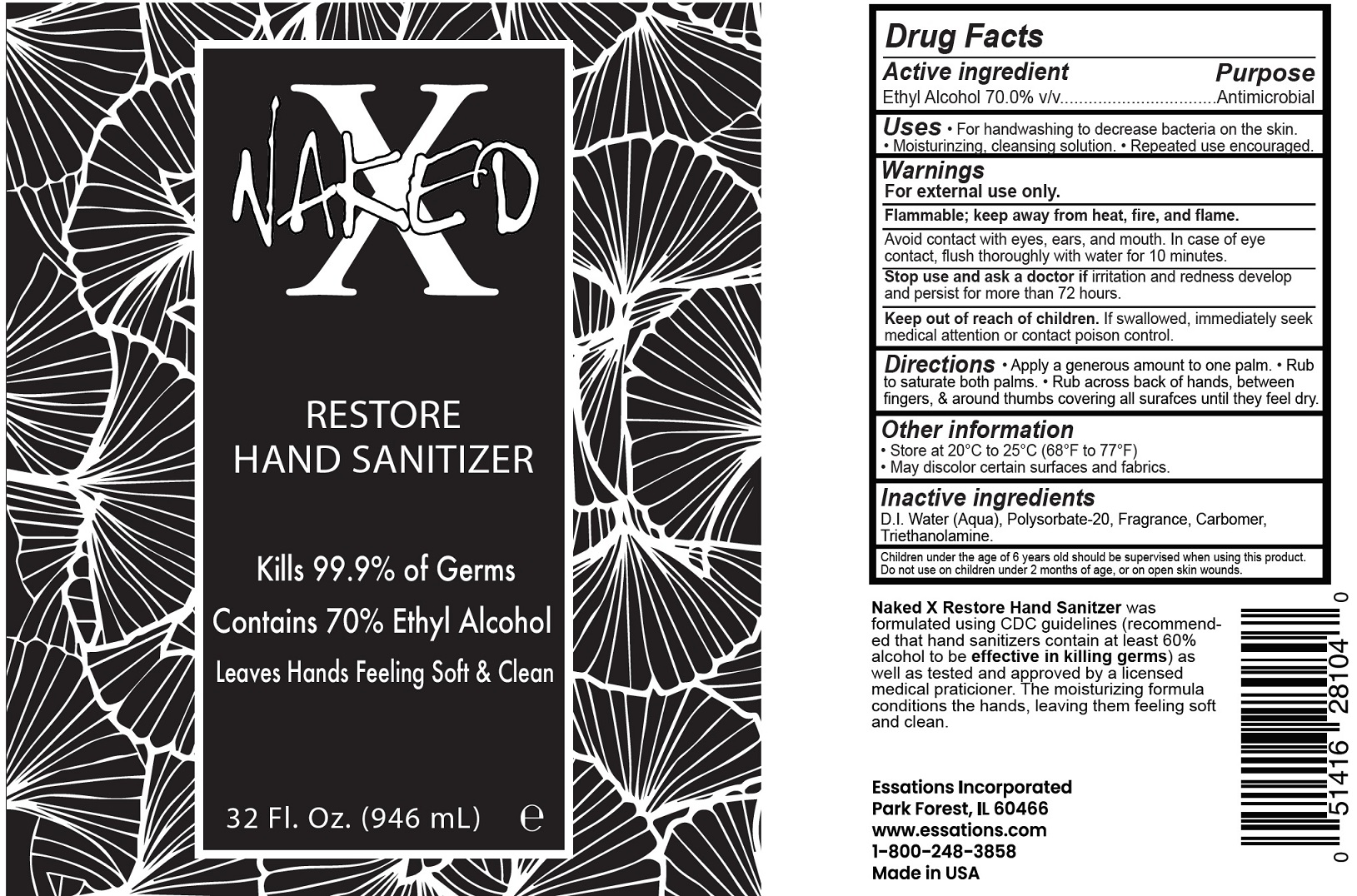 DRUG LABEL: Naked X Restore Hand Sanitizer
NDC: 79116-000 | Form: GEL
Manufacturer: Essations Inc.
Category: otc | Type: HUMAN OTC DRUG LABEL
Date: 20230120

ACTIVE INGREDIENTS: ALCOHOL 0.7 mL/1 mL
INACTIVE INGREDIENTS: WATER; POLYSORBATE 20; CARBOMER HOMOPOLYMER, UNSPECIFIED TYPE; TROLAMINE

Naked X Restore Hand Sanitizer

Active ingredient

Ethyl Alcohol 70.0% v/v

Purpose

Antimicrobial

Uses

• For handwashing to decrease bacteria on the skin. • Moisturinzing, cleansing solution. • Repeated use encouraged.

Warnings

For external use only.

Flammable; keep away from heat, fire, and flame.

Avoid contact with eyes, ears, and mouth. In case of eye contact, flush thoroughly with water for 10 minutes.

Stop use and ask a doctor if

irritation and redness develop and persist for more than 72 hours.

Keep out of reach of children.

If swallowed, immediately seek medical attention or contact poison control.

Directions

• Apply a generous amount to one palm. • Rub to saturate both palms. • Rub across back of hands, between fingers, & around thumbs covering all surafces until they feel dry.

Other information

• Store at 20°C to 25°C (68°F to 77°F)
• May discolor certain surfaces and fabrics.

Inactive ingredients

D.I. Water (Aqua), Polysorbate-20, Fragrance, Carbomer, Triethanolamine.

Children under the age of 6 years old should be supervised when using this product. Do not use on children under 2 months of age, or on open skin wounds.